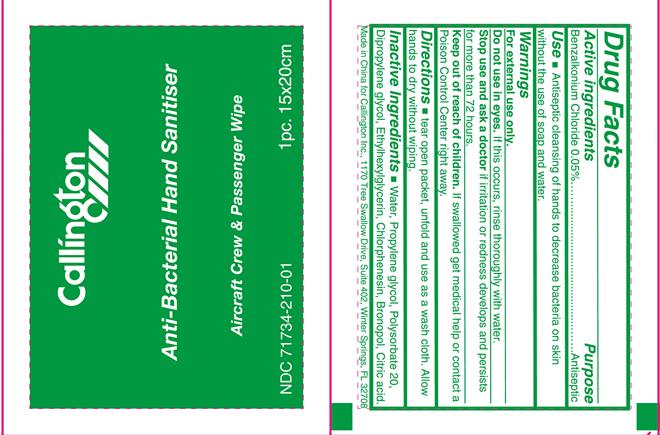 DRUG LABEL: Callington Anti-Bacterial Hand Sanitiser
NDC: 71734-210 | Form: CLOTH
Manufacturer: JIANGMEN SHUIZIRUN SANITARY ARTICLES CO., LTD.
Category: otc | Type: HUMAN OTC DRUG LABEL
Date: 20190225

ACTIVE INGREDIENTS: BENZALKONIUM CHLORIDE 0.05 g/1 g
INACTIVE INGREDIENTS: PROPYLENE GLYCOL; POLYSORBATE 20; Water; DIPROPYLENE GLYCOL; ETHYLHEXYLGLYCERIN; CHLORPHENESIN; BRONOPOL

DRUG FACTS

Active Ingredient

BENZALKONIUM CHLORIDE .......... 0.05%

Purpose

Antiseptic

Uses:

Antiseptic cleansing of hands to decrease bacteria on skin without the use of soap and water.

WARNINGS

For external use only.

- for external use only.
- do not use in eyes. If this occurs, rinse thoroughly with water.
- Stop use and ask a doctor if irritation o redness develops and persists for more than 72 hours.

Keep out of reach of children.

if swallowed get medical help or contact a Poison Control Center right away.

Directions

Tear open packedt, unfold and use as wash cloth. Allow hands to dry without wiping.

Inactive Ingredients:

Water, Propylene glycol, Polysorbate 20, Dipropylene glycol, Ethylhexylglycerin, Chlorphenesin, Bronopol, Citric acid.